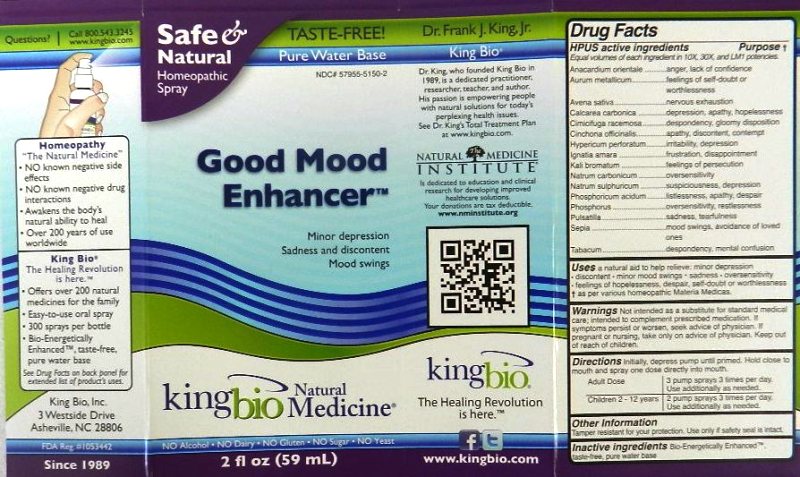 DRUG LABEL: Good Mood Enhancer
NDC: 57955-5150 | Form: LIQUID
Manufacturer: King Bio Inc.
Category: homeopathic | Type: HUMAN OTC DRUG LABEL
Date: 20120209

ACTIVE INGREDIENTS: SEMECARPUS ANACARDIUM JUICE 10 [hp_X]/59 mL; GOLD 10 [hp_X]/59 mL; AVENA SATIVA FLOWERING TOP 10 [hp_X]/59 mL; OYSTER SHELL CALCIUM CARBONATE, CRUDE 10 [hp_X]/59 mL; BLACK COHOSH 10 [hp_X]/59 mL; CINCHONA OFFICINALIS BARK 10 [hp_X]/59 mL; HYPERICUM PERFORATUM 10 [hp_X]/59 mL; STRYCHNOS IGNATII SEED 10 [hp_X]/59 mL; POTASSIUM BROMIDE 10 [hp_X]/59 mL; SODIUM CARBONATE 10 mL/59 mL; SODIUM SULFATE 10 [hp_X]/59 mL; PHOSPHORIC ACID 10 [hp_X]/59 mL; PHOSPHORUS 10 [hp_X]/59 mL; PULSATILLA VULGARIS 10 [hp_X]/59 mL; SEPIA OFFICINALIS JUICE 10 [hp_X]/59 mL; TOBACCO LEAF 10 [hp_X]/59 mL
INACTIVE INGREDIENTS: WATER

Good Mood Enhancer

Active Ingredients

HPUS active ingredients

Equal volumes of each ingredient in 10X, 30X, and LM1 potencies.

Anacardium orientale

Aurum metallicum

Avena sativa

Calcarea carbonica

Cimicifuga racemosa

Cinchona officinalis

Hypericum perforatum

Ignatia amara

Kali bromatum

Natrum carbonicum

Natrum sulphuricum

Phosphoricum acidum

Phosphorus

Pulsatilla

Sepia

Tabacum

Reference image good mood.jpg

Inactive Ingredient

Bio-Energetically Enhanced, taste-free, pure water base.

Reference image good mood.jpg

Indications and Usage

Uses a natural aid to help relieve: minor depression, discontent, minor mood swings, sadness, oversensitivity, feelings of hopelessness, despair, self-doubt or worthlessness.

As per various homeopathic Materia Medicas.

Reference image good mood.jpg

Warnings

Not intended as a substitute for standard medical care; intended to complement prescribed medication. If symptoms persist or worsen, seek advice of physician. If pregnant or nursing, take only on advice of physician. Keep out of reach of children.

Other Information

Tamper resistant for your protection. Use only if safety seal is intact.

Reference image good mood.jpg

Keep out of reach of children.
Reference image good mood.jpg

Dosage and Administration

Directions Initially, Depress pump until primed. Hold close to mouth and spray one dose directly into mouth.

Adult dose 3 pump sprays 3 times per day. Use additionally as needed.

Children 2 - 12 years 2 pump sprays 3 times per day. Use additionally as needed.

Reference image good mood.jpg

Purpose

HPUS active ingredients Purpose

Equal volumes of each ingredient in 10X, 30X, and LM1 potencies.

Anacardium orientale................................................anger, lack of confidence

Aurum metallicum.....................................................feeling of self-doubt or worthlessness

Avena sativa............................................................nervous exhaustion

Calcarea carbonica...................................................depression, apathy, hopelessness

Cimicifuga racemosa.................................................despondency, gloomy disposition

Cinchona officinalis....................................................apathy, discontent, contempt

Hypericum perforatum...............................................irritability, depression

Ignatia amara............................................................frustration, disappointment

Kali bromatum...........................................................feelings of persecution

Natrum carbonicum...................................................oversensitivity

Natrum sulphuricum...................................................suspiciousness, depression

Phosphoricum acidum................................................listlessness, apathy, despair

Phosphorus...............................................................oversensitivity, restlessness

Pulsatilla....................................................................sadness, tearfulness

Sepia........................................................................mood swings, avoidance of loved ones

Tabacum..................................................................despondency, mental confusion

Reference image good mood.jpg

PACKAGE LABEL

King Bio Inc.

3 Westside Drive

Asheville, NC 28806

www.kingbio.com

Questions? Call 800.543.3245

Safe and Natural Homeopathic spray